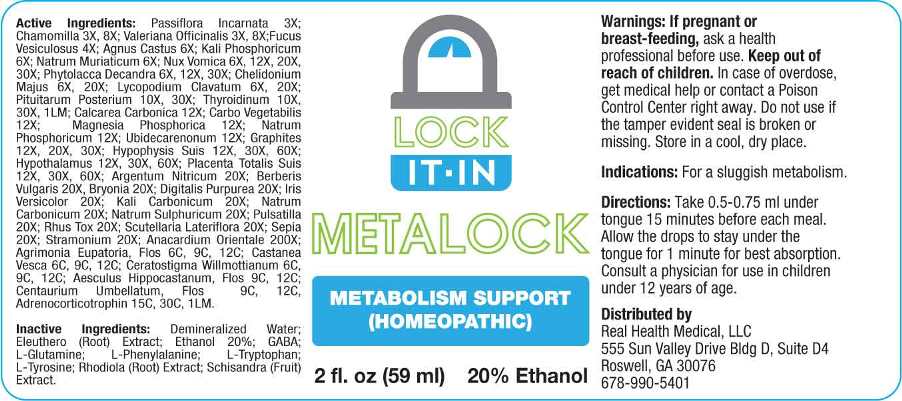 DRUG LABEL: Metalock
NDC: 72190-0002 | Form: LIQUID
Manufacturer: Real Health Medical, LLC
Category: homeopathic | Type: HUMAN PRESCRIPTION DRUG LABEL
Date: 20240122

ACTIVE INGREDIENTS: PASSIFLORA INCARNATA FLOWERING TOP 3 [hp_X]/1 mL; MATRICARIA CHAMOMILLA WHOLE 3 [hp_X]/1 mL; VALERIAN 3 [hp_X]/1 mL; FUCUS VESICULOSUS 4 [hp_X]/1 mL; CHASTE TREE FRUIT 6 [hp_X]/1 mL; DIBASIC POTASSIUM PHOSPHATE 6 [hp_X]/1 mL; SODIUM CHLORIDE 6 [hp_X]/1 mL; STRYCHNOS NUX-VOMICA SEED 6 [hp_X]/1 mL; PHYTOLACCA AMERICANA ROOT 6 [hp_X]/1 mL; CHELIDONIUM MAJUS WHOLE 6 [hp_X]/1 mL; LYCOPODIUM CLAVATUM SPORE 6 [hp_X]/1 mL; BOS TAURUS PITUITARY GLAND, POSTERIOR 10 [hp_X]/1 mL; THYROID, BOVINE 10 [hp_X]/1 mL; THYROID, OVINE 1 [hp_C]/1 mL; OYSTER SHELL CALCIUM CARBONATE, CRUDE 12 [hp_X]/1 mL; ACTIVATED CHARCOAL 12 [hp_X]/1 mL; MAGNESIUM PHOSPHATE, DIBASIC TRIHYDRATE 12 [hp_X]/1 mL; SODIUM PHOSPHATE, DIBASIC, HEPTAHYDRATE 12 [hp_X]/1 mL; UBIDECARENONE 12 [hp_X]/1 mL; GRAPHITE 12 [hp_X]/1 mL; SUS SCROFA PITUITARY GLAND 12 [hp_X]/1 mL; BOS TAURUS HYPOTHALAMUS 12 [hp_X]/1 mL; SUS SCROFA PLACENTA 12 [hp_X]/1 mL; SILVER NITRATE 20 [hp_X]/1 mL; BERBERIS VULGARIS ROOT BARK 20 [hp_X]/1 mL; BRYONIA ALBA ROOT 20 [hp_X]/1 mL; DIGITALIS 20 [hp_X]/1 mL; IRIS VERSICOLOR ROOT 20 [hp_X]/1 mL; POTASSIUM CARBONATE 20 [hp_X]/1 mL; SODIUM SULFATE 20 [hp_X]/1 mL; PULSATILLA VULGARIS WHOLE 20 [hp_X]/1 mL; TOXICODENDRON PUBESCENS LEAF 20 [hp_X]/1 mL; SCUTELLARIA LATERIFLORA WHOLE 20 [hp_X]/1 mL; SEPIA OFFICINALIS JUICE 20 [hp_X]/1 mL; DATURA STRAMONIUM 20 [hp_X]/1 mL; SEMECARPUS ANACARDIUM JUICE 200 [hp_X]/1 mL; AGRIMONIA EUPATORIA FLOWER 6 [hp_C]/1 mL; CASTANEA SATIVA LEAF 6 [hp_C]/1 mL; CERATOSTIGMA WILLMOTTIANUM FLOWER 6 [hp_C]/1 mL; AESCULUS HIPPOCASTANUM FLOWER 9 [hp_C]/1 mL; CENTAURIUM ERYTHRAEA FLOWER 9 [hp_C]/1 mL; CORTICOTROPIN 15 [hp_C]/1 mL
INACTIVE INGREDIENTS: .GAMMA.-AMINOBUTYRIC ACID; GLUTAMINE; PHENYLALANINE; TRYPTOPHAN; TYROSINE; ELEUTHERO; SCHISANDRA CHINENSIS FRUIT; SEDUM ROSEUM ROOT; WATER; ALCOHOL

DRUG FACTS:

ACTIVE INGREDIENTS:

Passiflora Incarnata 3X, Chamomilla 3X, 8X, Valeriana Officinalis 3X, 8X, Fucus Officinalis 4X, Agnus Castus 6X, Kali Phosphoricum 6X, Natrum Muriaticum 6X, 12X, Nux Vomica 6X, 12X, 20X, 30X, Phytolacca Decandra 6X, 12X, 30X, Chelidonium Majus 6X, 20X, Lycopodium Clavatum 6X, 20X, Pituitarum Posterium (Bovine) 10X, 30X, Thyroidinum (Bovine) 10X, 30X, Thyroidinum (Ovine) 1LM, Calcarea Carbonica 12X, Carbo Vegetabilis 12X, Magnesia Phosphorica 12X, Natrum Phosphoricum 12X, Ubidecarenonum 12X, Graphites 12X, 20X, 30X, Hypophysis Suis 12X, 30X, 60X, Hypothalamus (Bovine) 12X, 30X, 60X, Placenta Totalis Suis 12X, 30X, 60X, Argentum Nitricum 20X, Berberis Vulgaris 20X, Bryonia (Alba) 20X, Digitalis Purpurea 20X, Iris Versicolor 20X, Kali Carbonicum 20X, Natrum Carbonicum 20X , Natrum Sulphuricum 20X, Pulsatilla (Vulgaris) 20X, Rhus Tox 20X, Scutellaria Lateriflora 20X, Sepia 20X, Stramonium 20X, Anacardium Orientale 200X, Agrimonia Eupatoria, Flos 6C, 9C, 12C, Castanea Vesca 6C, 9C, 12C, Ceratostigma Willmottianum (Flos) 6C, 9C, 12C, Aesculus Hippocastanum, Flos 9C, 12C, Centaurium Umbellatum, Flos 9C, 12C, Adrenocorticotrophin 15C, 30C, 1LM.

INDICATIONS:

For a sluggish metabolism.

WARNINGS:

If pregnant or breast-feeding, ask a health professional before use.

Keep out of reach of children. In case of overdose, contact a physician or a Poison Control Center right away.

Do not use if the tamper evident seal is broken or missing.

Store in a cool, dry place.

Keep out of reach of children. In case of overdose, contact a physician or a Poison Control Center right away.

DIRECTIONS:

Take .05-0.75 ml under the tongue 15 minutes before each meal. Allow the drops to stay under the tongue for 1 minute for best absorption. Consult a physician for use in children under 12 years of age.

INDICATIONS:

For a sluggish metabolism.

INACTIVE INGREDIENTS:

GABA (Gamma Aminobutyric Acid), L-Glutamine, L-Phenylalanine, L-Tryptophan, L-Tyrosine, Eleuthero (Root), Schisandra (Fruit), Rhodiola (Root), Demineralized Water, Ethyl Alcohol

QUESTIONS:

Distributed by

Real Health Medical, LLC

555 Sun Valley Drive Bldg D, Suite D4

Roswell, GA 30076

678-990-5401

PACKAGE LABEL DISPLAY:

LOCK

IT-IN

METALOCK

METABOLISM SUPPORT

(HOMEOPATHIC)

2 fl. oz. (59 ml)